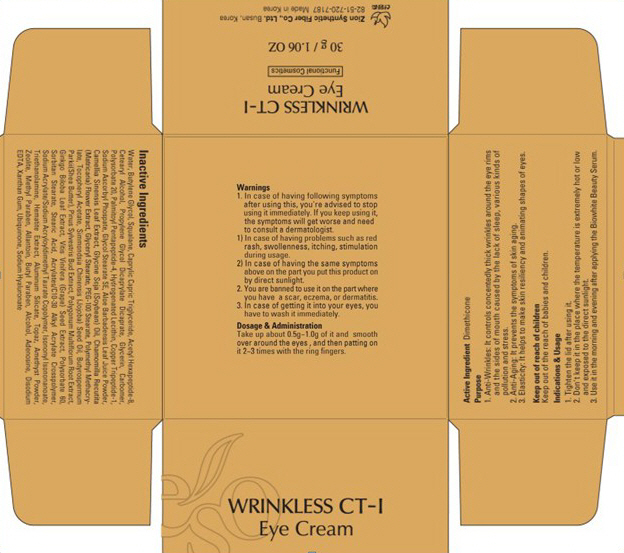 DRUG LABEL: WRINKLESS CT-1
NDC: 44781-150 | Form: CREAM
Manufacturer: ZION SYNTHETIC FIBER CO., LTD.
Category: otc | Type: HUMAN OTC DRUG LABEL
Date: 20110829

ACTIVE INGREDIENTS: DIMETHICONE 0.3 g/30 g
INACTIVE INGREDIENTS: Water; Butylene Glycol; Squalane; MEDIUM-CHAIN TRIGLYCERIDES; CETOSTEARYL ALCOHOL; Glycerin; CARBOMER 934; POLYSORBATE 20; Sodium Ascorbyl Phosphate; GLYCOL STEARATE; ALOE VERA LEAF; GLYCERYL MONOSTEARATE; POLYSORBATE 60; SORBITAN MONOSTEARATE; Stearic Acid; TROLAMINE; Aluminum Silicate; METHYLPARABEN; Allantoin; BUTYLPARABEN; Alcohol; REGRELOR; EDETATE DISODIUM; Xanthan Gum; HYALURONATE SODIUM

Drug Facts

Active ingredient: DIMETHICONE

Inactive ingredients:

Water, Butylene Glycol, Squalane, Caprylic Capric Triglyceride, Acetyl Hexapeptide-8, CETOSTEARYL ALCOHOL, Propylene Glycol Dicaprylate Dicaprate, Glycerin, Carbomer, Polysorbate 20, Palmitoyl Pentapeptide-4, Hydrogenated Lecithin, Copper Tripeptide-1, Sodium Ascorbyl Phosphate, Glycol Stearate SE, Aloe Barbadensis Leaf Juice Powder, Camellia Sinensis Leaf Extract, Glycine Soja (Soybean) Oil, Chamomilla Recutita (Matricaria) Flower Extract, Glyceryl Stearate, PEG-100 Stearate, Polymethyl Methacrylate, Tocopheryl Acetate, Simmondsia Chinensis (Jojoba)Seed Oil, Butyrospermum Parkii(Shea Butter), Pinus Sylvestris Bud Extract, Polygonum Multiflorum Root Extract, Ginkgo Biloba Leaf Extract, Vitis Vinifera (Grape) Seed Extract, Polysorbate 60, Sorbitan Stearate, Stearic Acid, Acrylates/C10-30 Alkyl Acrylate Crosspolymer, Sodium Acrylate/Sodium Acryloyldimethyl Taurate Copolymer, Isononyl Isononanoate, Triethanolamine, Hematite Extract, Aluminum Silicate, Topaz, Amethyst Powder, Zeolite, Methyl Paraben, Allantoin, Butyl Paraben, Alcohol, Adenosine, Disodium EDTA, Xanthan Gum, Ubiquinone, Sodium Hyaluronate

Purpose:
It controls concentedly thick wrinkles around the eye rims and the sides of mouth caused by the lack of sleep, various kinds of pollution and stress.
And it helps to make skin resiliency and animating shapes of eyes.

Warnings:
In case of having following symptoms after using this, you're advised to stop using it immediately. If you keep using it, the symptoms will get worse and need to consult a dermatologist.
- In case of having problems such as red rash, swollenness, itching, stimulation during usage.
- In case of having the same symptoms above on the part you put this product on by direct sunlight.
You are banned to use it on the part where you have a scar, eczema, or dermatitis.
In case of getting it into your eyes, you have to wash it immediately.

Keep out of reach of children:
Keep out of the reach of babies and children.

Indication and usage:
Tighten the lid after using it.
Don't keep it in the place where the temperature is extremely hot or low and exposed to the direct sunlight.
Use it in the morning and evening after applying the Biowhite Beauty Serum.

Dosage and administration:
Take up about 0.5g - 1.0g of it and smooth over around the eyes, and then patting on it 2-3 times with the ring fingers.